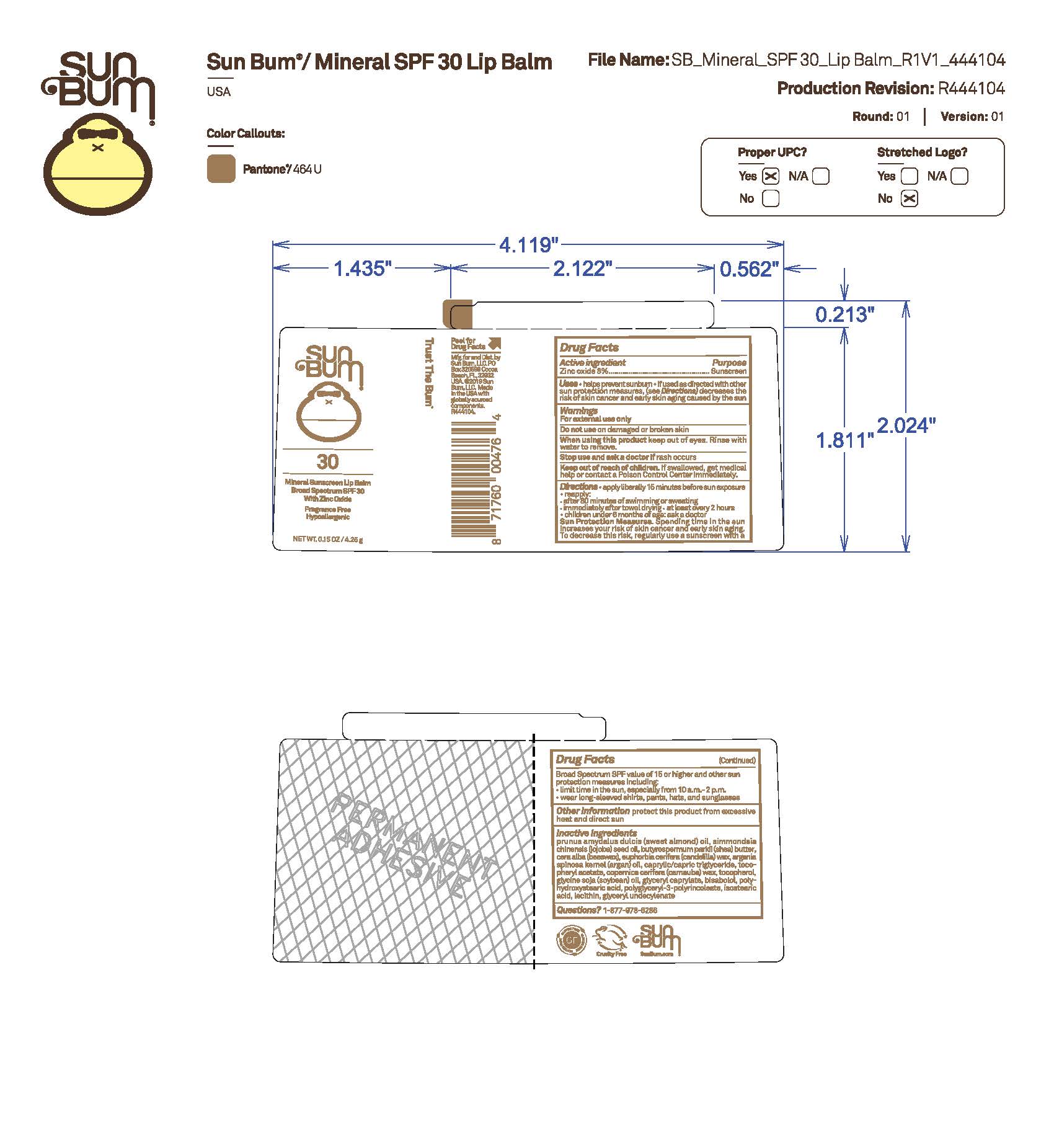 DRUG LABEL: Sun Bum 30 Mineral Sunscreen Lip Balm
NDC: 69039-813 | Form: STICK
Manufacturer: Sun Bum, LLC
Category: otc | Type: HUMAN OTC DRUG LABEL
Date: 20250819

ACTIVE INGREDIENTS: ZINC OXIDE 80 mg/1 g
INACTIVE INGREDIENTS: PRUNUS AMYGDALUS DULCIS (SWEET ALMOND) OIL; SIMMONDSIA CHINENSIS (JOJOBA) SEED OIL; POLYGLYCEROL POLYRICINOLEIC ACID; BISABOLOL; BUTYROSPERMUM PARKII (SHEA) BUTTER; COPERNICIA CERIFERA (CARNAUBA) WAX; GLYCERYL CAPRYLATE; POLYHYDROXYSTEARIC ACID (2300 MW); LECITHIN, SUNFLOWER; TOCOPHEROL; EUPHORBIA CERIFERA (CANDELILLA) WAX; ARGANIA SPINOSA KERNEL OIL; CAPRYLIC/CAPRIC TRIGLYCERIDE; SOYBEAN OIL; BEESWAX; GLYCERYL 1-UNDECYLENATE; ISOSTEARIC ACID; .ALPHA.-TOCOPHEROL ACETATE

Sun Bum 30 Mineral Sunscreen Lip Balm

Active Ingredients

Zinc Oxide 8%

Purpose

Sunscreen

Uses

• helps prevent sunburn • if used as directed with other sun protection measures, (see Directions) decreases the risk of skin cancer and early skin aging caused by the sun

Warnings

• apply liberally 15 minutes before sun exposure

• reapply: • after 80 minutes of swimming or sweating • immediately after towel drying • at least every 2 hours

• children under 6 months of age: ask a doctor

• Sun Protection Measures. Spending time in the sun increases your risk of skin cancer and early skin aging. To decrease this risk, regularly use a sunscreen with a Broad Spectrum SPF value of 15 or higher and other sun protection measures including:

• limit time in the sun, especially from 10 a.m.- 2 p.m.

• wear long-sleeved shirts, pants, hats and sunglasses

Warnings

Keep Out Of Reach Of Children

Directions

• apply liberally 15 minutes before sun exposure

• reapply: • after 80 minutes of swimming or sweating • immediately after towel drying • at least every 2 hours

• children under 6 months of age: ask a doctor

• Sun Protection Measures. Spending time in the sun increases your risk of skin cancer and early skin aging. To decrease this risk, regularly use a sunscreen with a Broad Spectrum SPF value of 15 or higher and other sun protection measures including:

• limit time in the sun, especially from 10 a.m.- 2 p.m.

• wear long-sleeved shirts, pants, hats and sunglasses

Directions

• apply liberally 15 minutes before sun exposure

Other Information

protect this product from excessive heat and direct sun

Inactive Ingredients

prunus amygdalus dulcis (sweet almond) oil, simmondsia chinensis (jojoba) seed oil, butyrospermum parkii (shea) butter, cera alba (beeswax), euphorbia cerifera (candelilla) wax, argania spinosa kernel (argan) oil, caprylic/capric triglyceride, tocopheryl acetate, copernica cerifera (carnauba) wax, tocopherol, glycine soja (soybean) oil, glyceryl caprylate, bisabolol, polyhydroxystearic acid, polyglyceryl-3 polyricinoleate, isostearic acid, lecithin, glyceryl undecylenate

Questions?

1-877-978-6286